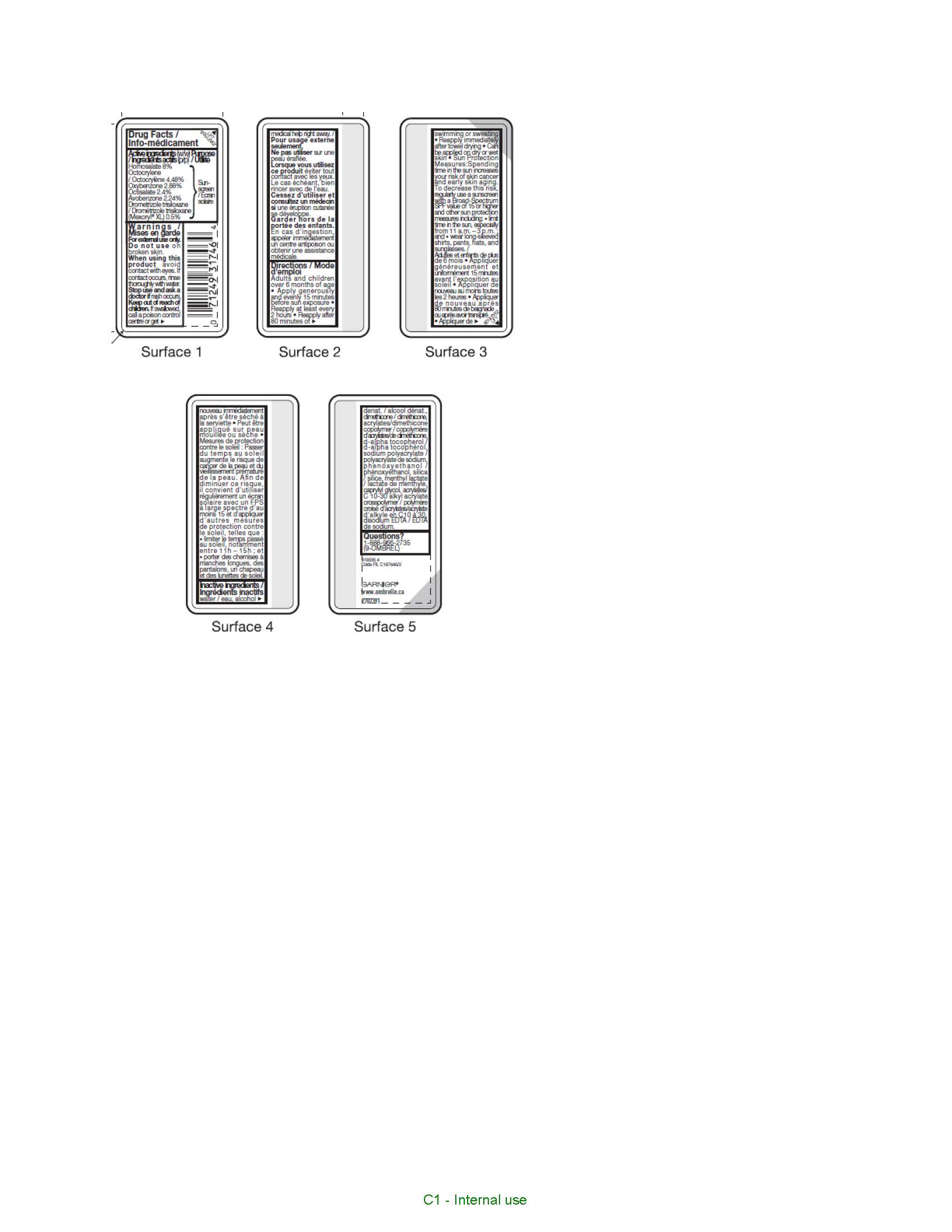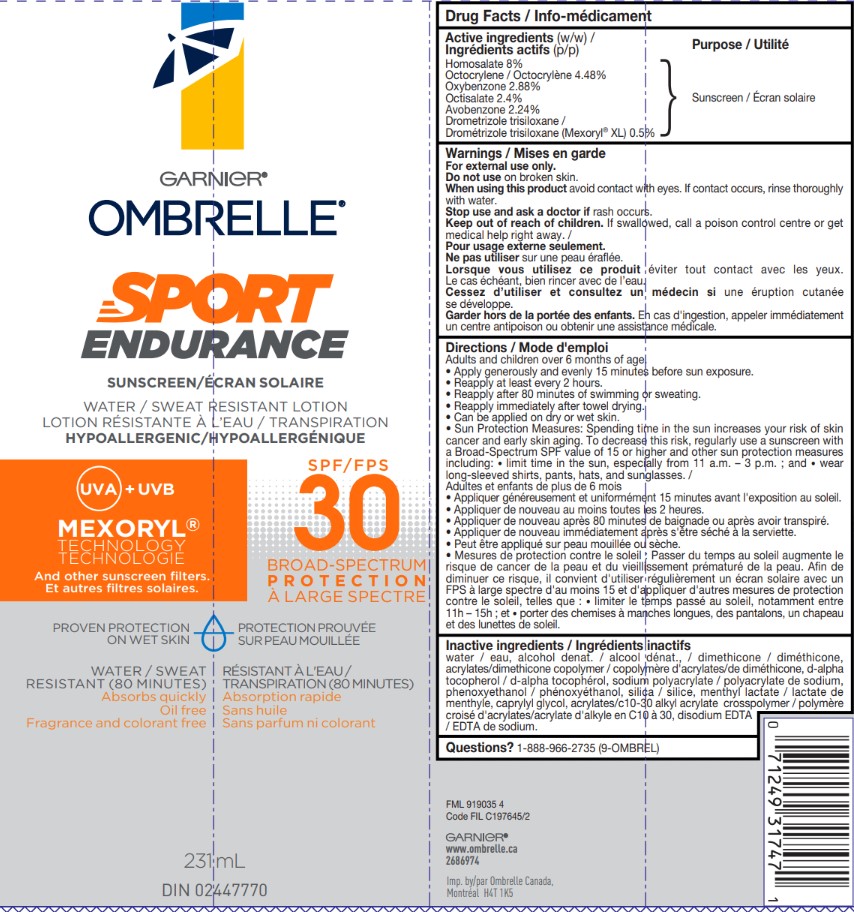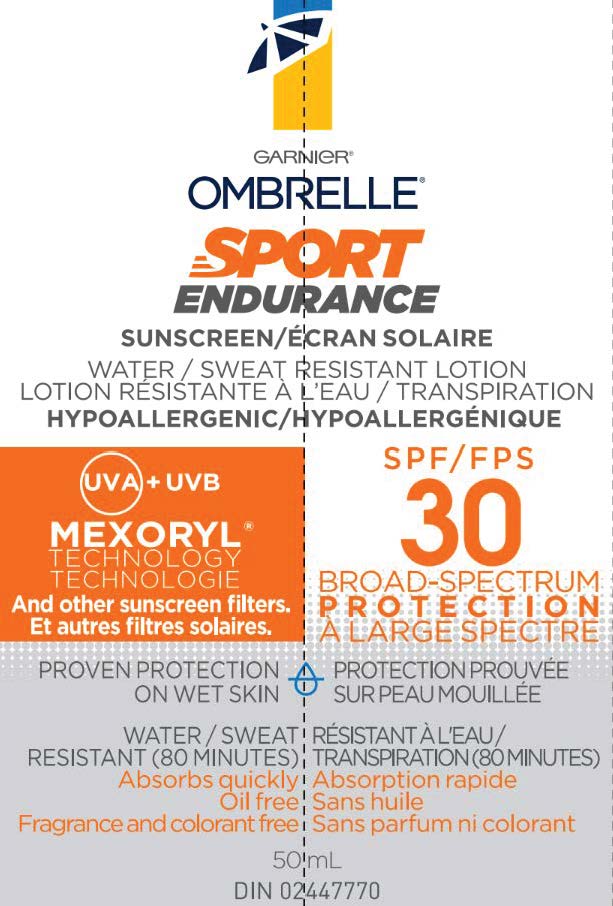 DRUG LABEL: Garnier Ombrelle SPF 30 Sport Endurance Water Resistant
NDC: 49967-747 | Form: LOTION
Manufacturer: L'Oreal USA Products Inc
Category: otc | Type: HUMAN OTC DRUG LABEL
Date: 20260107

ACTIVE INGREDIENTS: AVOBENZONE 22.4 mg/1 mL; DROMETRIZOLE TRISILOXANE 5 mg/1 mL; HOMOSALATE 80 mg/1 mL; OCTISALATE 24 mg/1 mL; OCTOCRYLENE 44.8 mg/1 mL; OXYBENZONE 28.8 mg/1 mL
INACTIVE INGREDIENTS: WATER; ALCOHOL; DIMETHICONE; TOCOPHEROL; SODIUM POLYACRYLATE (8000 MW); PHENOXYETHANOL; SILICA DIMETHYL SILYLATE; METHYL LACTATE, (-)-; CAPRYLYL GLYCOL; CARBOMER INTERPOLYMER TYPE A (ALLYL SUCROSE CROSSLINKED); EDETATE DISODIUM

Drug Facts

Active ingredients

Avobenzone 2.24%

Drometrizole Trisiloxane 0.5%

Homosalate 8%

Octisalate 2.4%

Octocrylene 4.48%

Oxybenzone 2.88%

Warnings

For external use only. Do not use on damaged or broken skin. If rash occurs, discontinue use and consult a health care practitioner. Keep out of eyes. Rinse with water to remove. Keep out of reach of children. If swallowed, get medical help or contact a Poison Control Center right away.

Directions

Apply generously and evenly 15 minutes before sun exposure. Reapply at least every 2 hours, after 80 minutes of swimming or sweating and immediately after towel drying. For use on children less than 6 months of age, consult a health care practitioner.

Inactive ingredients

water, alcohol denat., dimethicone, tocopherol, sodium polyacrylate, phenoxyethanol, silica, menthyl lactate, caprylyl glycol, acrylates/dimethicone copolymer, acrylates/C10-30 alkyl acrylate crosspolymer, disodium EDTA